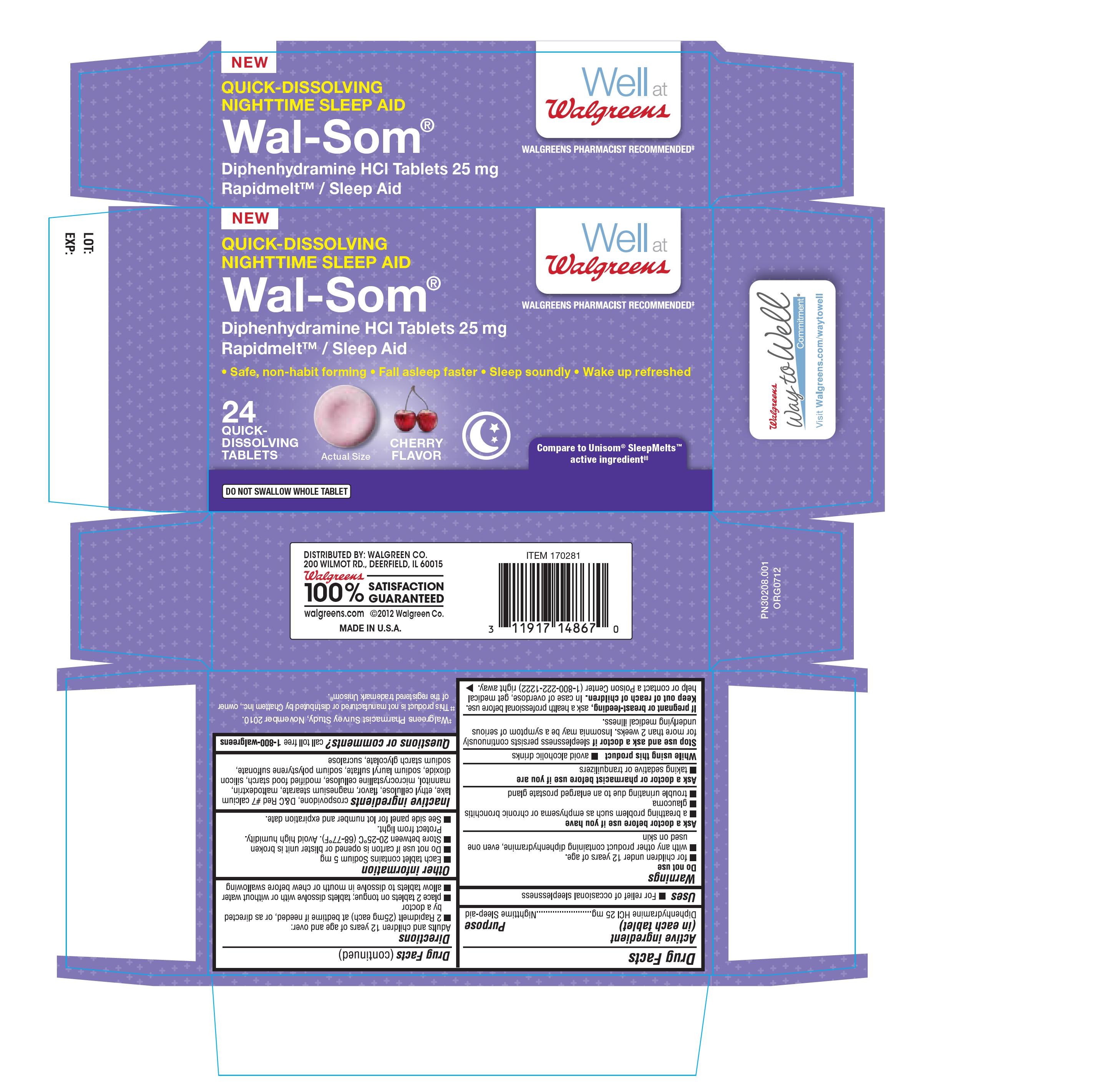 DRUG LABEL: Wal-Som
                
NDC: 0363-0223 | Form: TABLET
Manufacturer: Walgreen 
Category: otc | Type: HUMAN OTC DRUG LABEL
Date: 20120822

ACTIVE INGREDIENTS: DIPHENHYDRAMINE HYDROCHLORIDE 25 mg/1 1
INACTIVE INGREDIENTS: CROSPOVIDONE; D&C RED NO. 7; ETHYLCELLULOSES; MAGNESIUM STEARATE; MALTODEXTRIN; MANNITOL; CELLULOSE, MICROCRYSTALLINE; SILICON DIOXIDE; SODIUM LAURYL SULFATE; SODIUM POLYSTYRENE SULFONATE; SODIUM STARCH GLYCOLATE TYPE A POTATO; SUCRALOSE; MODIFIED CORN STARCH (1-OCTENYL SUCCINIC ANHYDRIDE)

Drug facts

Active ingredient

Diphenhydramine HCl 25mg

Purpose

Nighttime Sleep-aid

Uses

For relief of occasional sleeplessness

Warnings

Do not use

- For children under 12 years of age
- With any other product containing Diphenhydramine, even one used on skin

Ask a doctor before use if you have

- a breathing problem such as emphysema or chronic bronchitis
- glaucoma
- trouble urinating due to an enlarged prostate gland

Ask a doctor or pharmacist before use if you are

- Taking sedatives or tranquilizers

While using this product

avoid alcoholic drinks

Stop use and ask a doctor if

sleeplessness persists continuously for more than 2 weeks. Insomnia may be a symptom of serious underlying medical illness.

If pregnant or breast-feeding

ask a health professional before use

Keep out of reach of children

In case of overdose, get medical help or contact a poison center (1-800-222-1222) right away

Directions

Adults and children 12 years of age and over:

- 2 Rapidmelt (25mg each) at bedtime if needed, or as directed by a doctor
- Place 2 tablets on to tongue; tablets dissolve with or without water
- allow tablets to dissolve in mouth or chew before swallowing

Other information

- Each tablet contains Sodium 5mg
- Do not use if carton is opened or blister unit is broken
- Store between 20-25 °C(68-77°F). Avoid high humidity. Protect from light.
- See side panel for lot number and expiration date

Inactive ingredients

crospovidone, D&C Red No 7 calcium lake, ethyl cellulose, flavor, magnesium stearate, maltodextrin, mannitol, microcrystalline cellulose, modified food starch, silicon dioxide, sodium lauryl sulfate, sodium polystyrene sulfonate, sodium starch glycolate, sucralose

Question or comments?

Call toll free 1--800-walgreens

Principal display panel

NEW

QUICK DISSOLVING

NIGHTTIME SLEEP AID

WELL AT WALGREENS

WALGREENS PHARMACIST RECOMMENDED

WAL-SOM

DIPHENHYDRAMINE HCL TABLETS 25MG

RAPIDMELT/ SLEEP AID

SAFE, NON-HABIT FORMING, FALL ASLEEP FASTER, SLEEP SOUNDLY, WAKE UP REFRESHED

24 QUICK DISSOLVING TABLETS

COMPARE TO UNISOM SLEEPMELTS ACTIVE INGREDIENT

DO NOT SWALLOW WHOLE TABLET